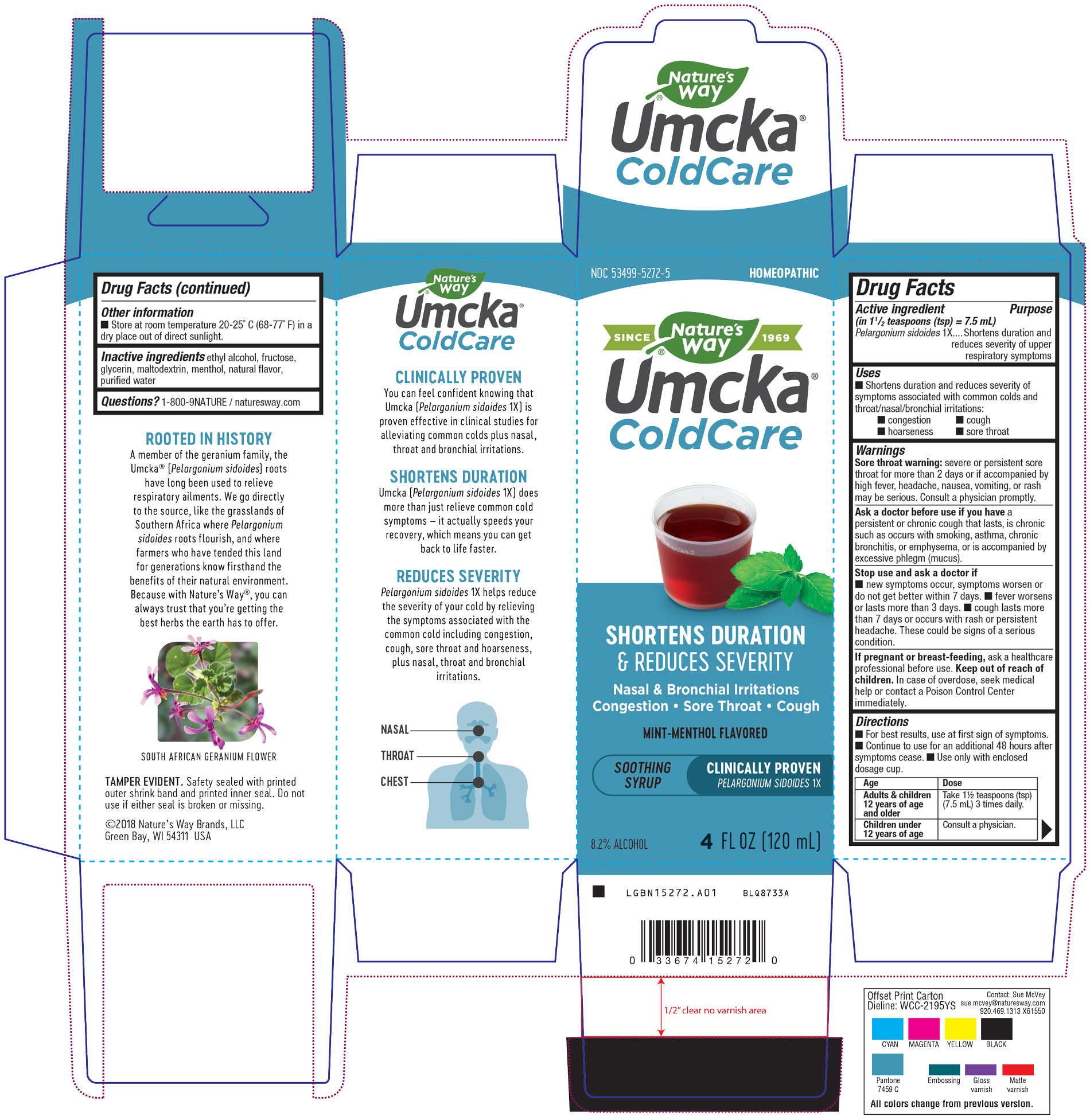 DRUG LABEL: Umcka Menthol
NDC: 53499-5272 | Form: SYRUP
Manufacturer: Schwabe North America, Inc
Category: homeopathic | Type: HUMAN OTC DRUG LABEL
Date: 20251124

ACTIVE INGREDIENTS: PELARGONIUM SIDOIDES ROOT 1 [hp_X]/120 mL
INACTIVE INGREDIENTS: ALCOHOL; FRUCTOSE; MENTHOL; WATER; GLYCERIN; MALTODEXTRIN

Umcka Mint-Menthol Syrup

Active Ingredient

Pelargonium sidoides 1X

Inactive Ingredient

Ethyl Alcohol

Fructose

Glycerin

Maltodextrin

Menthol

Natural Flavor

Purified Water

Dosage & Administration

Directions

For best results, use at first sign of symptoms.

Continue to use for an additional 48 hours after symptoms cease

Use only with enclosed dosage cup.

Adults & children 12 years of age and older: Take 1 ½ teaspoon (tsp) (7.5 mL) 3 times daily.

Children under 12 years of age: Consult a physician.

Indications & Usage

Shortens duration and reduces severity of symptoms associated with common colds and throat/nasal/bronchial irritations: congestion, cough, hoarseness, sore throat.

Purpose

Shortens duration and reduces severity of symptoms associated with common colds and throat/nasal/bronchial irritations: congestion, cough, hoarseness, sore throat.

Warnings

Sore throat warning: severe or persistent sore throat for more than 2 days or if accompanied by a high fever, headache, nausea, vomiting, or rash may be serious.

Consult a physician promptly.

Ask Doctor

Ask a doctor before use if you have a persistent or chronic cough that lasts, is chronic such as occurs with smoking, asthma, chronic bronchitis, or emphysema, or is accompanied by excessive phlegm (mucus).

Stop Use

Stop use and ask the doctor if new symptoms occur, symptoms worsen or do not get better within 7 days, fever worsens or lasts more than 3 days, or cough lasts more than 7 days or occurs with rash or persistent headache.

These could be signs of a serious condition.

Pregnancy or Breast Feeding

If pregnant or breast-feeding, ask a healthcare professional before use.

Keep out of reach of children.

Overdose

In case of overdose, seek medical help or contact a Poison Control Center immediately.